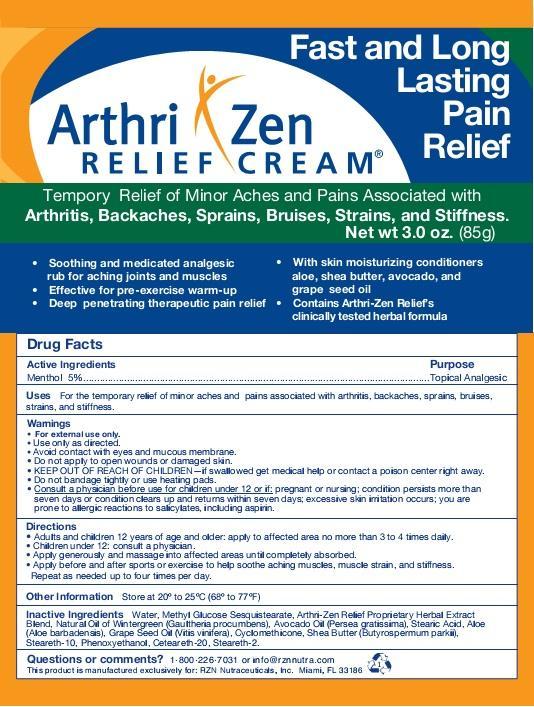 DRUG LABEL: Arthri-Zen Relief 
                
NDC: 34876-001 | Form: CREAM
Manufacturer: RZN Nutraceuticals, Inc.
Category: otc | Type: HUMAN OTC DRUG LABEL
Date: 20131220

ACTIVE INGREDIENTS: MENTHOL 5 g/100 g
INACTIVE INGREDIENTS: WATER; GAULTHERIA PROCUMBENS TOP; AVOCADO OIL; STEARIC ACID; ALOE VERA LEAF; GRAPE SEED OIL; CYCLOMETHICONE; SHEA BUTTER; STEARETH-10; PHENOXYETHANOL; POLYOXYL 20 CETOSTEARYL ETHER; STEARETH-2

Drug Facts

Active Ingredients

Menthol 5%

Purpose

Menthol 5%.......................................Topical Analgesic

Uses

For the temporary relief of minor aches and pains associated with arthritis, backaches, sprains, bruises, strains, and stiffness.

Warnings

- For external use only.
- Use only as directed.
- Avoid contact with eyes and mucous membranes.

DO NOT USE

Do not apply to open wounds or damaged skin.

KEEP OUT OF REACH OF CHILDREN

OTHER SAFETY INFORMATION

– if swallowed get medical help or contact a poison
center right away.

• Do not bandage tightly or use with heating pads.

ASK DOCTOR

Consult a physician before use for children under 12 or if; pregnant or nursing;
condition persists more than seven days or condition clears
up and returns within seven days; excessive skin
irritation occurs; you are prone to allergic
reactions to salicylates, including aspirin.

Directions

• Adults and children under 12 years of age and older: apply to affected area
no more than 3 to 4 times daily.
• Children under 12: consult a physician.
• Apply generously and massage into affected areas
until completely absorbed.
• Apply before and after sports or exercise to help soothe aching muscles, muscle strain, and stiffness.

Repeat as needed up to four times a day.

Other Information

Store at 20º to 25º C (68º to 77º F)

Inactive Ingredients

Water, Methyl Glucose Sesquistearate, Arthri-Zen Relief Proprietary Herbal Extract
Blend, Natural Oil of Wintergreen (Gaultheria procumbens), Avocado Oil (Persea gratissima), Stearic Acid, Aloe
(Aloe barbadensis), Grape Seed Oil (Vitis vinifera), Cyclomethicone, Shea Butter (Butyrospermum parkii),
Steareth-10, Phenoxyethanol, Ceteareth-20, Steareth-2.

Questions or comments?

1-800-226-7031 or info@rznnutra.com

DESCRIPTION

This product is manufactured exclusively for: RZN Nutraceuticals, Inc. Miami, FL 33186
• Soothing and medicated analgesic
rub for aching joints and muscles
• Effective for pre-exercise warm-up
• Deep penetrating therapeutic pain relief
• With skin moisturizing conditioners
aloe, shea butter, avocado, and
grape seed oil
• Contains Arthri-Zen Relief’s
clinically tested herbal formula

Principal Display Panel

Fast and Long Lasting

Pain Relief

Arthri Zen

RELIEF CREAM

Temporary Relief of Minor Aches and Pains Associated with
Arthritis, Backaches, Sprains, Bruises, Strains, and Stiffness.

Net wt 3.0 oz.(85g)